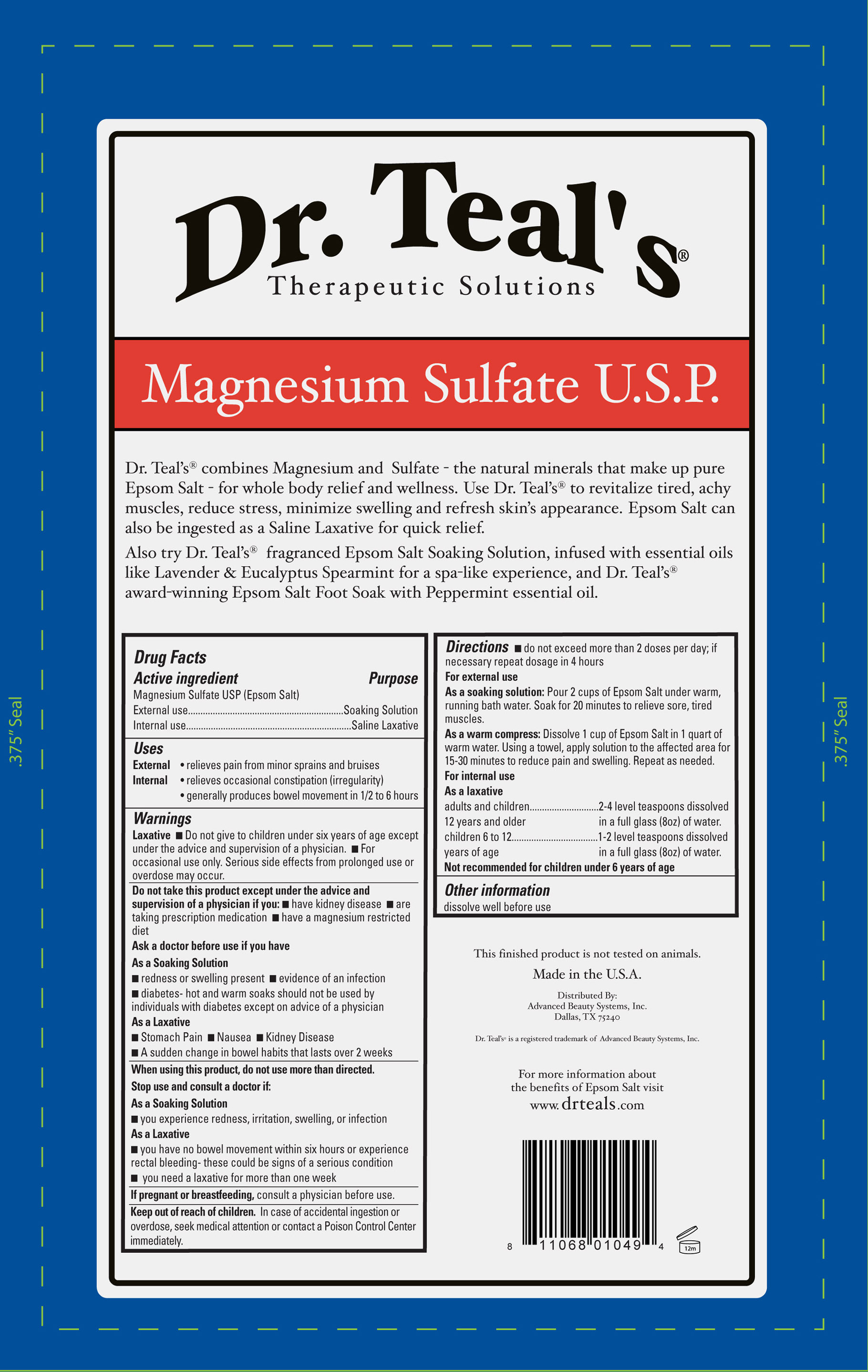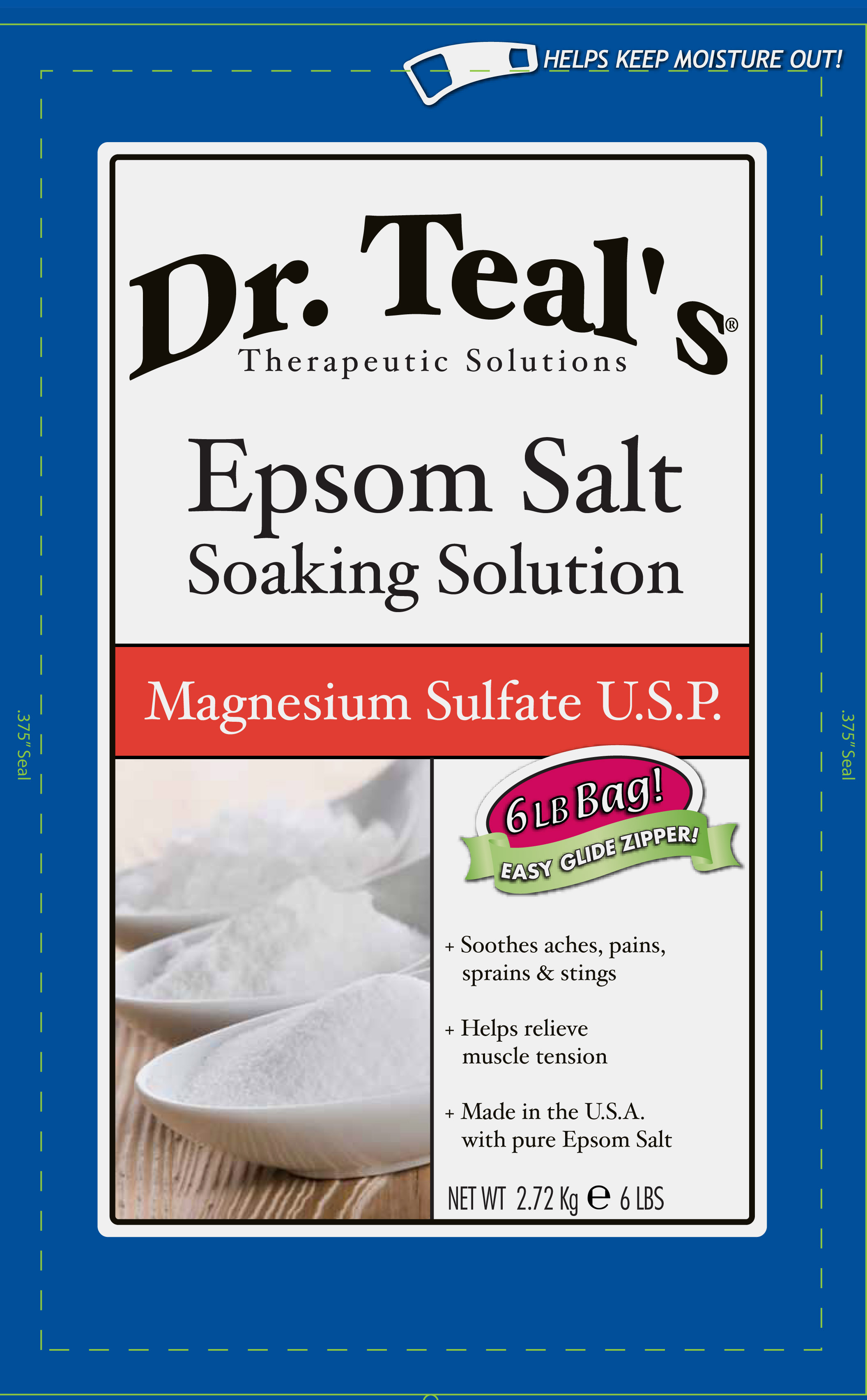 DRUG LABEL: Epsom Salt
NDC: 51345-099 | Form: GRANULE
Manufacturer: Advanced Beauty Systems, Inc.
Category: otc | Type: HUMAN OTC DRUG LABEL
Date: 20120620

ACTIVE INGREDIENTS: MAGNESIUM SULFATE 2.72 kg/2.72 kg

Dr. Teals Magnesium sulfate U.S.P.

Active ingredient Purpose

Magnesium Sulfate USP (Epsom Salts)

External use Soaking solution

Internal Use Saline Laxative

Uses

External: Relieves pain from minor sprains and bruises

Internal: Relieves occasional constipation (irregularity)

generally produces bowel movement in 1/2 to 6 hours.

Keep out of reach of children. In case of accidental ingestion or overdose, seek medical attention or contact a Poison Control Center immediately.

When using this product, do not use more than directed.

Stop use and consult a doctor if:

As a soaking solution

- you experience redness, irritation, swelling , or infection

As a laxative

- you have no bowel movements within six hours or experience rectal bleeding-these could be signs of a serious condition

- you need a laxative for more than a week

Warnings:

Laxative
- Do not give to children under six years of age except under the advice and supervision of a physician.
- For occasional use only. Serious side effects from prolonged use or overdose may occur.
Do not take this product except under the advice and supervision of a physician if you:
- Have kidney disease
- Are taking prescription medication
- Have a magnesium restricted diet
Ask a doctor before if you have
As a soaking solution
- redness or swelling present
- evidence of an infection
- diabetes - hot and warm soaks should not be used by individuals with diabetes except on advice of a physician
As a laxative
- Stomach pain
- Nausea
- Kidney disease
- A sudden change in bowel habits that lasts over 2 weeks
If pregnant or breast feeding, consult a physician before use
Other information
Dissolve before use

Directions

- Do not exceed more than 2 doses per day, if neccessary repeat dosage in 4 hours

For External use

As a soaking solution: pour 2 cups of Epsom Salts under warm, running bath water. Soak for 20 minutes for to relieve sore,tired muscles.

As a warm compress: Dissolve 1 cup of Epsom Salts in 1 quart of warm water. Using a towel, apply solution to the affected area for 15-30 minutes to reduce pain and and swelling. Repeat as needed.
For internal use
As a laxative 2-4 level teaspoons dissolved in a full glass (8oz) of water.
adults and children 12 years and older
children 6 to 12 years of age 1-2 level teaspoons dissolved in a full glass (8oz) of water.
not recommended for children under 6 years of age

This product contains no inactive ingredients

PACKAGE LABEL

Dr. Teal's

Therapeutic solutions
Epsom Salt Soaking Solution
Magnesium Sulfate USP
Sooths aches, pains, sprains and stings
Helps relieve muscle tension
Made in U.S.A. with pure Epsom Salt
Net Wt. 2.72 Kg 6 lbs